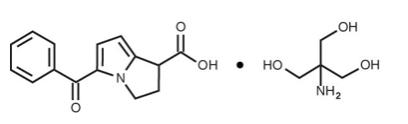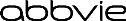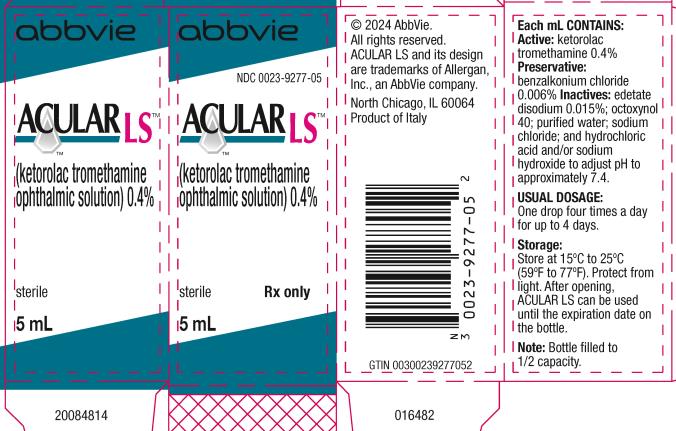 DRUG LABEL: ACULAR LS
NDC: 0023-9277 | Form: SOLUTION/ DROPS
Manufacturer: Allergan, Inc.
Category: prescription | Type: HUMAN PRESCRIPTION DRUG LABEL
Date: 20240621

ACTIVE INGREDIENTS: KETOROLAC TROMETHAMINE 4 mg/1 mL
INACTIVE INGREDIENTS: EDETATE DISODIUM; OCTOXYNOL-40; WATER; SODIUM CHLORIDE; BENZALKONIUM CHLORIDE; HYDROCHLORIC ACID; SODIUM HYDROXIDE

HIGHLIGHTS OF PRESCRIBING INFORMATION

These highlights do not include all the information needed to use ACULAR LS safely and effectively. See full prescribing information for ACULAR LS.
ACULAR LS® (ketorolac tromethamine ophthalmic solution) 0.4%,
for topical ophthalmic use
Initial U.S. Approval: 1991

1 INDICATIONS AND USAGE

ACULAR LS ophthalmic solution is a nonsteroidal, anti-inflammatory drug (NSAID) indicated for the reduction of ocular pain and burning/stinging following corneal refractive surgery. (1)

2 DOSAGE AND ADMINISTRATION

One drop of ACULAR LS should be applied in the operated eye 4 times per day as needed for pain and burning/stinging for up to 4 days following corneal refractive surgery. (2.1)

3 DOSAGE FORMS AND STRENGTHS

Ophthalmic solution containing ketorolac tromethamine 0.4% (4 mg/mL). (3)

4 CONTRAINDICATIONS

Hypersensitivity to any component of this product. (4)

5 WARNINGS AND PRECAUTIONS

- Delayed healing (5.1)
- Cross-sensitivity or hypersensitivity (5.2)
- Increased bleeding time due to interference with thrombocyte aggregation (5.3)
- Corneal effects including keratitis (5.4)

6 ADVERSE REACTIONS

The most common adverse reactions occurring in 1 - 5% of patients included conjunctival hyperemia, corneal infiltrates, headache, ocular edema and ocular pain. (6.1)

To report SUSPECTED ADVERSE REACTIONS, contact AbbVie at 1-800-678-1605 or the FDA at 1-800-FDA-1088 or www.fda.gov/medwatch.

FULL PRESCRIBING INFORMATION

1 INDICATIONS AND USAGE

ACULAR LS ophthalmic solution is indicated for the reduction of ocular pain and burning/stinging following corneal refractive surgery.

2 DOSAGE AND ADMINISTRATION

2.1 Recommended Dosing

The recommended dose of ACULAR LS ophthalmic solution is one drop four times a day in the operated eye as needed for pain and burning/stinging for up to 4 days following corneal refractive surgery.

2.2 Use With Other Topical Ophthalmic Medications

ACULAR LS has been safely administered in conjunction with other topical ophthalmic medications such as alpha-agonists, antibiotics, beta-blockers, carbonic anhydrase inhibitors, cycloplegics, and mydriatics. Drops should be administered at least 5 minutes apart.

3 DOSAGE FORMS AND STRENGTHS

Ophthalmic solution containing ketorolac tromethamine 0.4% (4 mg/mL).

4 CONTRAINDICATIONS

ACULAR LS ophthalmic solution is contraindicated in patients with previously demonstrated hypersensitivity to any of the ingredients in the formulation [see Adverse Reactions (6.1)].

5 WARNINGS AND PRECAUTIONS

5.1 Delayed Healing

Topical nonsteroidal anti-inflammatory drugs (NSAIDs) may slow or delay healing. Topical corticosteroids are also known to slow or delay healing. Concomitant use of topical NSAIDs and topical steroids may increase the potential for healing problems.

5.2 Cross-Sensitivity or Hypersensitivity

There is the potential for cross-sensitivity to acetylsalicylic acid, phenylacetic acid derivatives, and other NSAIDs. There have been reports of bronchospasm or exacerbation of asthma associated with the use of ketorolac tromethamine ophthalmic solution in patients who have either a known hypersensitivity to aspirin/non-steroidal anti-inflammatory drugs or a past medical history of asthma. Therefore, caution should be used when treating individuals who have previously exhibited sensitivities to these drugs.

5.3 Increased Bleeding Time

With some NSAIDs, there exists the potential for increased bleeding time due to interference with thrombocyte aggregation. There have been reports that ocularly applied nonsteroidal anti-inflammatory drugs may cause increased bleeding of ocular tissues (including hyphemas) in conjunction with ocular surgery.

It is recommended that ACULAR LS ophthalmic solution be used with caution in patients with known bleeding tendencies or who are receiving other medications, which may prolong bleeding time.

5.4 Corneal Effects

Use of topical NSAIDs may result in keratitis. In some susceptible patients, continued use of topical NSAIDs may result in epithelial breakdown, corneal thinning, corneal erosion, corneal ulceration, or corneal perforation. These events may be sight threatening. Patients with evidence of corneal epithelial breakdown should immediately discontinue use of topical NSAIDs and should be closely monitored for corneal health.

Postmarketing experience with topical NSAIDs suggests that patients with complicated ocular surgeries, corneal denervation, corneal epithelial defects, diabetes mellitus, ocular surface diseases (e.g., dry eye syndrome), rheumatoid arthritis, or repeat ocular surgeries within a short period of time may be at increased risk for corneal adverse events which may become sight threatening. Topical NSAIDs should be used with caution in these patients.

Postmarketing experience with topical NSAIDs also suggests that use more than 1 day prior to surgery or use beyond 14 days post-surgery may increase patient risk for the occurrence and severity of corneal adverse events.

5.5 Risk of Contamination

Do not allow the tip of the bottle to contact the eye or surrounding structures because this could cause the tip to become contaminated by common bacteria known to cause ocular infections. Serious damage to the eye and subsequent loss of vision may result from using contaminated solutions.

5.6 Contact Lens Wear

ACULAR LS should not be administered while wearing contact lenses.

6 ADVERSE REACTIONS

The following serious adverse reactions are described elsewhere in the labeling:

- Delayed Healing [see Warnings and Precautions (5.1)]
- Cross-Sensitivity or Hypersensitivity [see Warnings and Precautions (5.2)]
- Increased Bleeding Time [see Warnings and Precautions (5.3)]
- Corneal Effects [see Warnings and Precautions (5.4)]

6.1 Clinical Trials Experience

Because clinical trials are conducted under widely varying conditions, adverse reaction rates observed in the clinical trials of a drug cannot be directly compared to rates in the clinical trials of another drug and may not reflect the rates observed in practice.

The most frequently reported adverse reactions for ACULAR LS ophthalmic solution occurring in approximately 1 to 5% of the overall study population were conjunctival hyperemia, corneal infiltrates, headache, ocular edema, and ocular pain.

The most frequent adverse reactions reported with the use of ketorolac tromethamine ophthalmic solutions have been transient stinging and burning on instillation. These reactions were reported by up to 40% of patients participating in clinical trials.

Other adverse reactions occurring approximately in 1 to 10% of the time during treatment with other ketorolac tromethamine ophthalmic solutions included allergic reactions (including eye swelling, eyelid edema, and hyperemia), corneal edema, iritis, ocular inflammation, ocular irritation, superficial keratitis, and superficial ocular infections.

Other adverse reactions reported rarely with the use of ketorolac tromethamine ophthalmic solutions included: corneal ulcer, eye dryness, and visual disturbance (blurry vision).

6.2 Postmarketing Experience

The following adverse reactions have been identified during postmarketing use of ketorolac tromethamine ophthalmic solutions in clinical practice. Because they are reported voluntarily from a population of unknown size, estimates of frequency cannot be made. The reactions, which have been chosen for inclusion due to either their seriousness, frequency of reporting, possible causal connection to topical ketorolac tromethamine ophthalmic solutions or a combination of these factors, include bronchospasm or exacerbation of asthma, corneal erosion, corneal perforation, corneal thinning and corneal melt, and epithelial breakdown [see Warnings and Precautions (5.2, 5.4)].

8 USE IN SPECIFIC POPULATIONS

8.1 Pregnancy

Risk Summary

There are no adequate or well-controlled studies with ACULAR LS in pregnant women. No evidence of teratogenicity has been observed in rats or rabbits with ACULAR LS at clinically relevant doses.

8.2 Lactation

Risk Summary

It is not known whether ketorolac when given topically is present in human milk. Because many drugs are excreted in human milk, caution should be exercised when ACULAR LS is administered to a nursing woman.

8.4 Pediatric Use

Safety and effectiveness of ketorolac tromethamine in pediatric patients below the age of 3 have not been established.

8.5 Geriatric Use

No overall differences in safety or effectiveness have been observed between elderly and other adult patients.

11 DESCRIPTION

ACULAR LS (ketorolac tromethamine ophthalmic solution) 0.4% is a member of the pyrrolo-pyrrole group of nonsteroidal anti-inflammatory drugs (NSAIDs) for ophthalmic use. Its chemical name is (±)-5-Benzoyl-2,3-dihydro-1H-pyrrolizine-1-carboxylic acid, compound with 2-amino-2-(hydroxymethyl)-1,3-propanediol (1:1), and its molecular weight is 376.40. Its molecular formula is C19H24N2O6 and it has the following structure:

ACULAR LS ophthalmic solution is supplied as a sterile isotonic aqueous 0.4% solution, with a pH of approximately 7.4. ACULAR LS ophthalmic solution contains a racemic mixture of R-(+) and S-(-)- ketorolac tromethamine. Ketorolac tromethamine may exist in three crystal forms. All forms are equally soluble in water. The pKa of ketorolac is 3.5. This white to off-white crystalline substance discolors on prolonged exposure to light. The osmolality of ACULAR LS ophthalmic solution is 290 mOsmol/kg.

Each mL of ACULAR LS ophthalmic solution contains: Active: ketorolac tromethamine 0.4%. Preservative: benzalkonium chloride 0.006%. Inactives: edetate disodium 0.015%; octoxynol 40; purified water; sodium chloride; and hydrochloric acid and/or sodium hydroxide to adjust pH.

12 CLINICAL PHARMACOLOGY

12.1 Mechanism of Action

Ketorolac tromethamine is a nonsteroidal anti-inflammatory drug which, when administered systemically, has demonstrated analgesic, anti-inflammatory, and anti-pyretic activity. The mechanism of its action is thought to be due to its ability to inhibit prostaglandin biosynthesis.

12.3 Pharmacokinetics

One drop of 0.5% ketorolac tromethamine ophthalmic solution was instilled into one eye and one drop of vehicle into the other eye TID in 26 healthy subjects. Five of 26 subjects had detectable concentrations of ketorolac in their plasma (range 11 to 23 ng/mL) at day 10 during topical ocular treatment.

Two drops of 0.5% ketorolac tromethamine ophthalmic solution instilled into the eyes of patients 12 hours and 1 hour prior to cataract extraction achieved a mean ketorolac concentration of 95 ng/mL in the aqueous humor of 8 of 9 eyes tested (range 40 to 170 ng/mL).

14 CLINICAL STUDIES

In two double-masked, multi-centered, parallel-group studies, 313 patients who had undergone photorefractive keratectomy received ACULAR LS 0.4% or its vehicle QID for up to 4 days. Significant differences favored ACULAR LS for the reduction of ocular pain and burning/stinging following photorefractive keratectomy surgery.

Results from clinical studies indicate that ketorolac tromethamine has no significant effect upon intraocular pressure.

The safety and effectiveness of ACULAR LS in post-cataract surgery patients has not been established.

16 HOW SUPPLIED/STORAGE AND HANDLING

ACULAR LS (ketorolac tromethamine ophthalmic solution) 0.4% is supplied sterile, in white opaque plastic LDPE bottles with white droppers, with a gray high impact polystyrene (HIPS) caps as follows:

5 mL in 10 mL bottle NDC 0023-9277-05

Storage: Store at 15oC to 25oC (59oF to 77oF). Protect from light. After opening, ACULAR LS can be used until the expiration date on the bottle.

17 PATIENT COUNSELING INFORMATION

Slow or Delayed Healing

Inform patients of the possibility that slow or delayed healing may occur while using nonsteroidal anti-inflammatory drugs (NSAIDs).

Avoiding Contamination of the Product

Instruct patients to avoid allowing the tip of the bottle to contact the eye or surrounding structures because this could cause the tip to become contaminated by common bacteria known to cause ocular infections. Serious damage to the eye and subsequent loss of vision may result from using contaminated solutions.

Contact Lens Wear

Advise patients that ACULAR LS ophthalmic solution should not be administered while wearing contact lenses.

Intercurrent Ocular Conditions

Advise patients that if they develop an intercurrent ocular condition (e.g., trauma or infection) or have ocular surgery, they should immediately seek their physician’s advice concerning the continued use of ACULAR LS.

Concomitant Topical Ocular Therapy

Advise patients that if more than one topical ophthalmic medication is being used, the medicines should be administered at least 5 minutes apart.

Distributed by:
AbbVie Inc.
North Chicago, IL 60064

© 2024 AbbVie. All rights reserved.
ACULAR LS and its design are trademarks of Allergan, Inc., an AbbVie company.

V2.1USPI9277

PACKAGE LABEL

Principal Display Panel

ALLERGAN™

NDC 0023-9277-05

ACULAR LS™

(ketorolac tromethamine
ophthalmic solution) 0.4%

sterile Rx only

5 mL